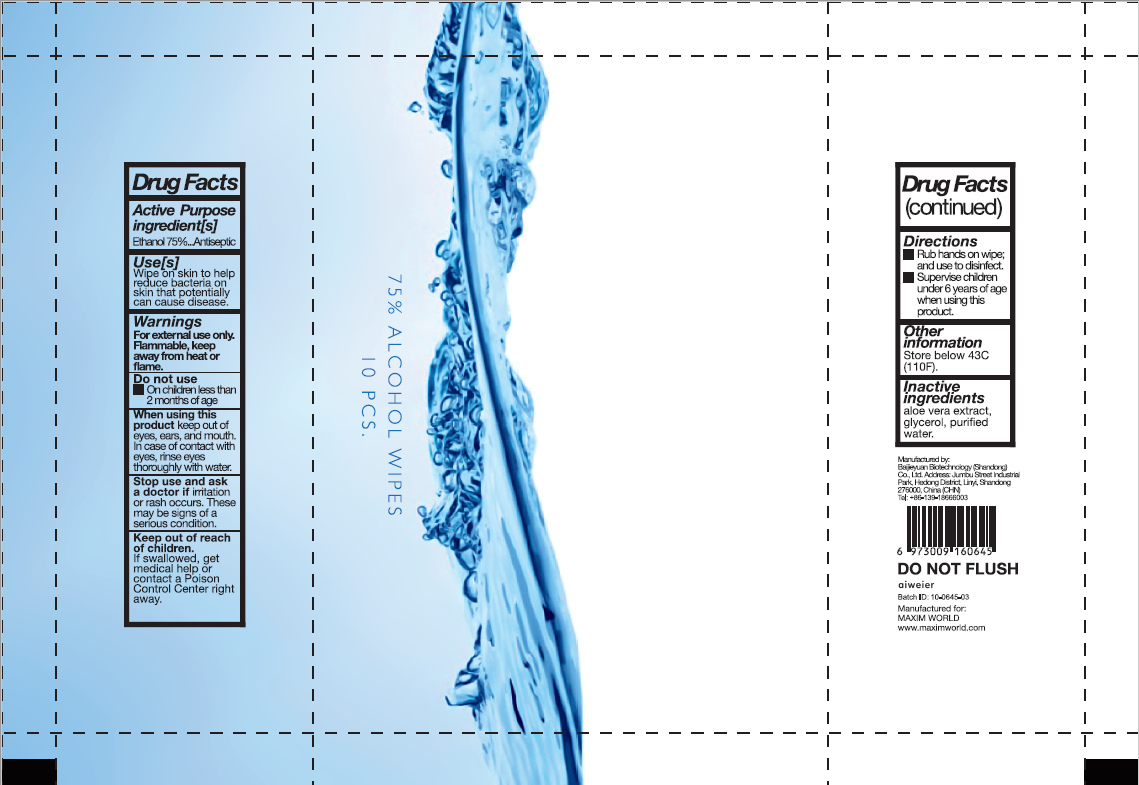 DRUG LABEL: 75% Alcohol wipes
NDC: 55490-029 | Form: CLOTH
Manufacturer: Baijieyuan Biotechnology (Shandong) Co., Ltd.
Category: otc | Type: HUMAN OTC DRUG LABEL
Date: 20230309

ACTIVE INGREDIENTS: ALCOHOL 75 mL/100 1
INACTIVE INGREDIENTS: ALOE; WATER; GLYCERIN

DOSAGE AND ADMINISTRATION

Store below 110°F (43°C)

INACTIVE INGREDIENT

Glycerol

Aloe extract

Pure water

INDICATIONS AND USAGE

Open the upper cover, cpen the unsealing glue, pull out the wet wipes,and dose the upper cover tightly to prevent the wet wipes from drying.

ACTIVE INGREDIENT

Ethyl alcohol

keep out of reach of children

PURPOSE

Disinfection
Sterilization
No Rinseing

WARNINGS

For external use only,Keep away from heat or flame.